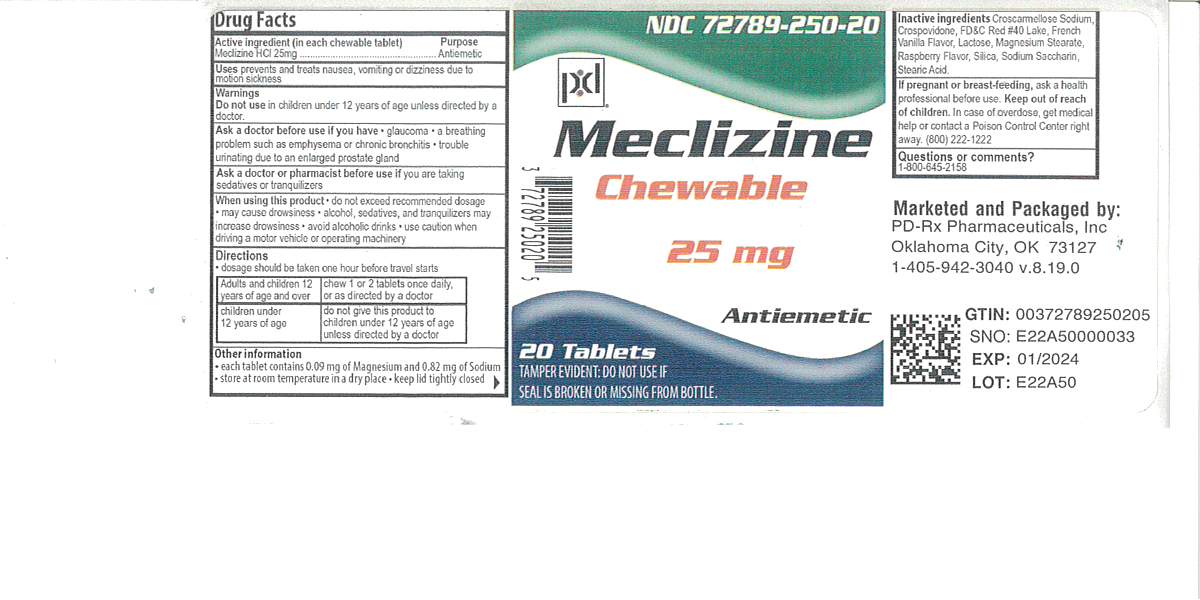 DRUG LABEL: Meclizine Hydrochloride
NDC: 72789-250 | Form: TABLET, CHEWABLE
Manufacturer: PD-Rx Pharmaceuticals, Inc.
Category: otc | Type: HUMAN OTC DRUG LABEL
Date: 20251008

ACTIVE INGREDIENTS: MECLIZINE HYDROCHLORIDE 25 mg/1 1
INACTIVE INGREDIENTS: CROSPOVIDONE; VANILLA; MAGNESIUM STEARATE; RASPBERRY; STEARIC ACID; SILICON DIOXIDE; FD&C RED NO. 40; LACTOSE MONOHYDRATE; SACCHARIN SODIUM; CROSCARMELLOSE SODIUM

Drug Facts

Active ingredient (in each chewable tablet)
Meclizine HCl 25 mg

Purpose
Antiemetic

Uses

prevents and treats nausea, vomiting or dizziness due to motion sickness

WARNINGS

Do not use in

children under 12 years of age unless directed by a doctor

Ask a doctor before use if you have

 glaucoma

 a breathing problem such as emphysema or chronic bronchitis
 trouble urinating due to an enlarged prostate gland

Ask a doctor or pharmacist before use if

you are taking sedatives or tranquilizers

When using this product

 Do not exceed recommended dosage

 may cause drowsiness

 alcohol, sedatives, and tranquilizers may increase drowsiness

 avoid alcoholic drinks
 use caution when driving a motor vehicle or operating machinery

PREGNANCY OR BREAST FEEDING

If pregnant or breast-feeding,ask a health professional before use.

Keep out of reach of children.

OVERDOSAGE

In case of overdose, get medical help or contact a Poison Control Center right away (1-800-222-1222).

Directions

 Dosage should be taken one hour before travel starts

adults and children 12 years of age and over | chew 1 to 2 tablets once daily, or as directed by a doctor
children under 12 years of age | do not give this product to children under 12 years of age unless directed by a doctor

Other information

 Store at room temperature in a dry place at 15°-30°C (59°-86°F)
 keep lid tightly closed

INACTIVE INGREDIENT

Croscarmellose Sodium, Crospovidone, FD&C Red #40 Lake, French Vanilla Flavor, Lactose, Magnesium Stearate, Raspberry Flavor, Silica, Sodium Saccharin, Stearic Acid

Questions or comments?

1-800-645-2158

TAMPER EVIDENT: DO NOT USE IF SEAL IS BROKEN OR MISSING FROM BOTTLE.

PACKAGE LABEL

Meclizine 25 mg

Antiemetic